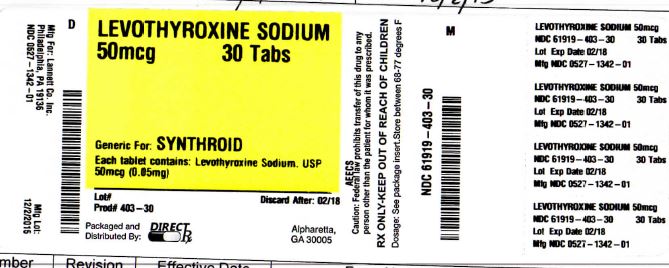 DRUG LABEL: LEVOTHYROXINE SODIUM
NDC: 61919-403 | Form: TABLET
Manufacturer: DirectRX
Category: prescription | Type: HUMAN PRESCRIPTION DRUG LABEL
Date: 20151203

ACTIVE INGREDIENTS: LEVOTHYROXINE SODIUM 0.05 mg/1 1
INACTIVE INGREDIENTS: SILICON DIOXIDE; MAGNESIUM STEARATE; CELLULOSE, MICROCRYSTALLINE; ACACIA; SODIUM STARCH GLYCOLATE TYPE A POTATO; LACTOSE; STARCH, CORN

LEVOTHYROXINE SODIUM